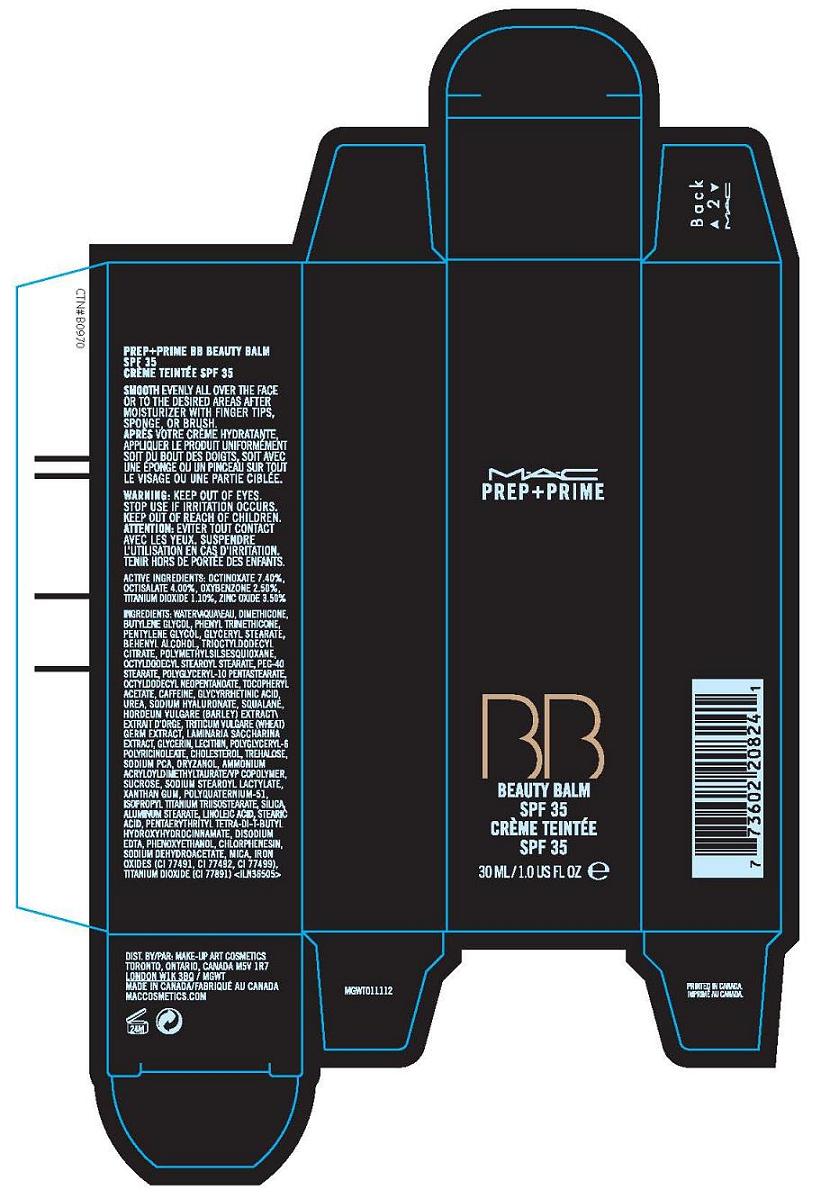 DRUG LABEL: PREP (plus) PRIME BEAUTY BALM
NDC: 40046-0036 | Form: CREAM
Manufacturer: MAKE-UP ART COSMETICS
Category: otc | Type: HUMAN OTC DRUG LABEL
Date: 20100514

ACTIVE INGREDIENTS: OCTINOXATE 7.4 mL/100 mL; OCTISALATE 4 mL/100 mL; OXYBENZONE 2.5 mL/100 mL; TITANIUM DIOXIDE 1.1 mL/100 mL; ZINC OXIDE 3.5 mL/100 mL

ACTIVE INGREDIENT

ACTIVE INGREDIENTS: OCTINOXATE 7.40% [] OCTISALATE 4.00% [] OXYBENZONE 2.50% [] TITANIUM DIOXIDE 1.10% [] ZINC OXIDE 3.50%

WHEN USING

DIRECTIONS:SMOOTH EVENLY ALL OVER THE FACE OR TO THE DESIRED AREA AFTER MOISTURIZER WITH FINGERTIPS, SPONGE OR BRUSH

WARNINGS

WARNING: KEEP OUT OF EYES. STOP USE IF IRRITATION OCCURS. KEEP OUT OF REACH OF CHILDREN.

PACKAGE LABEL

PRINCIPAL DISPLAY PANEL:

MAC

PREP + PRIME

BB

BEAUTY BALM

SPF 35

30 ML/1.0 US FL OZ

DIST. BY MAKEUP ART COSMETICS

TORONTO, ONTARIO CANADA M5V 1R7

MAC COSMETICS.COM